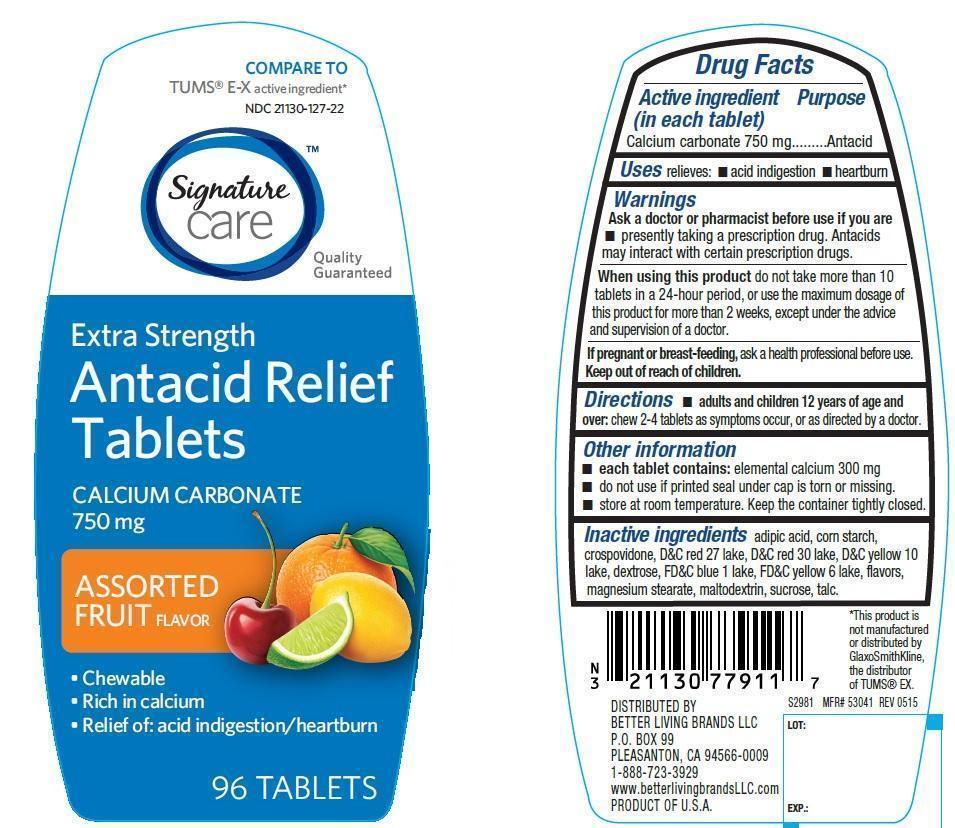 DRUG LABEL: Antacid Relief Extra Strength Assorted Fruit
NDC: 21130-127 | Form: TABLET, CHEWABLE
Manufacturer: Safeway
Category: otc | Type: HUMAN OTC DRUG LABEL
Date: 20220112

ACTIVE INGREDIENTS: CALCIUM CARBONATE 750 mg/1 1
INACTIVE INGREDIENTS: ADIPIC ACID; STARCH, CORN; CROSPOVIDONE; D&C RED NO. 27; D&C RED NO. 30; D&C YELLOW NO. 10; DEXTROSE, UNSPECIFIED FORM; FD&C BLUE NO. 1; FD&C YELLOW NO. 6; MAGNESIUM STEARATE; MALTODEXTRIN; SUCROSE; TALC

Extra Strength Antacid Relief Assorted Fruit

Active ingredient (in each tablet)

Calcium carbonate 750 mg

Purpose

Antacid

Uses

relieves

- acid indigestion
- heartburn

Warnings

Ask a doctor or pharmacist before use if you are

- presently taking a prescription drug. Antacids may interact with certain prescription drugs.

When using this product

do not take more than 10 tablets in a 24-hour period, or use the maximum dosage of this product for more than 2 weeks, except under the advice and supervision of a doctor.

If pregnant or breast-feeding, ask a health professional before use.

Keep out of reach of children

Directions

- adults and children 12 years of age and over: chew 2-4 tablets as symptoms occur, or as directed by a doctor.

Other information

- each tablet contains: elemental calcium 300 mg
- do not use if printed seal under cap is torn or missing.
- store at room temperature. keep the container tightly closed.

Inactive ingredients

adipic acid, corn starch, crospovidone, D&C red 27 lake, D&C red 30 lake, D&C yellow 10 lake, dextrose, FD&C blue 1 lake, FD&C yellow 6 lake, flavors, magnesium stearate, maltodextrin, sucrose, talc

PACKAGE LABEL

COMPARE TO TUMS® E-X active ingredient*

NDC21130-127-22

Signature Care

Extra Strength

Antacid Relief Tablets

CALCIUM CARBONATE 750 mg

ASSORTED FRUIT FLAVOR

- Chewable
- Rich in Calcium
- Relief of: Acid Indigestion/Heartburn

96 Tablets